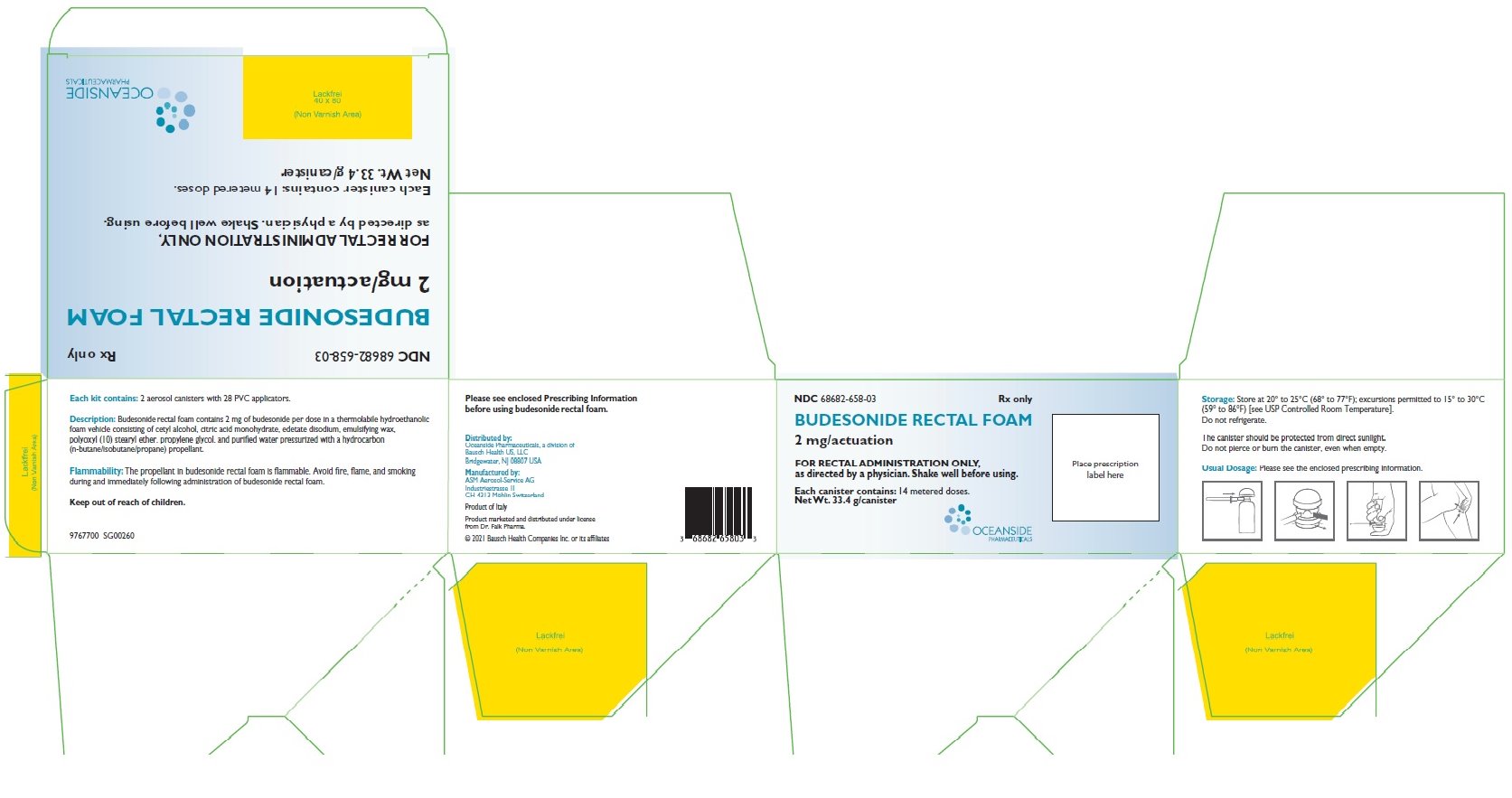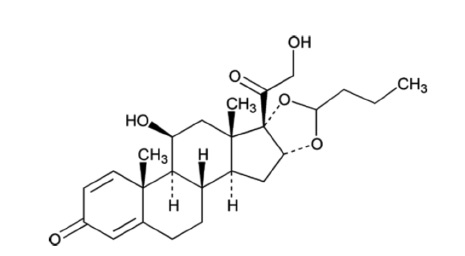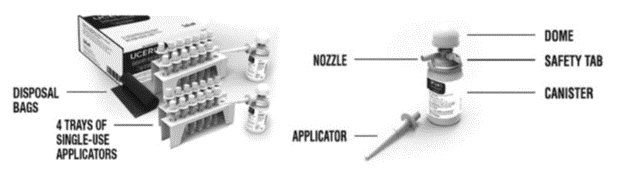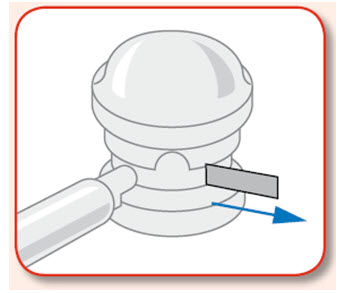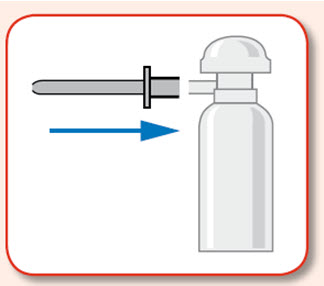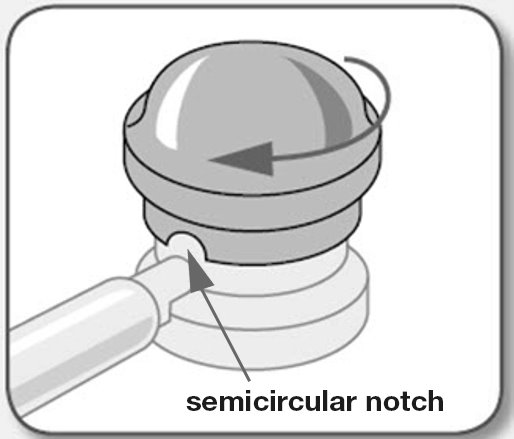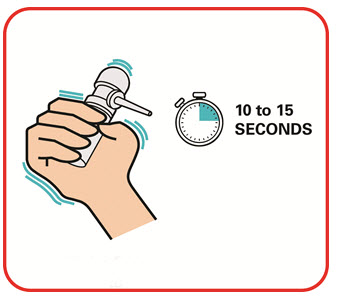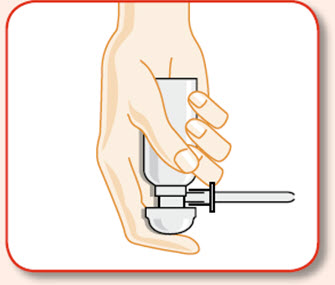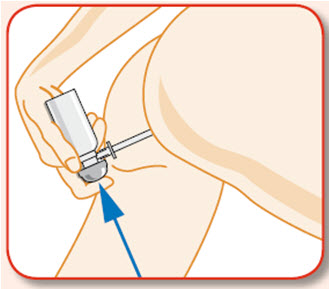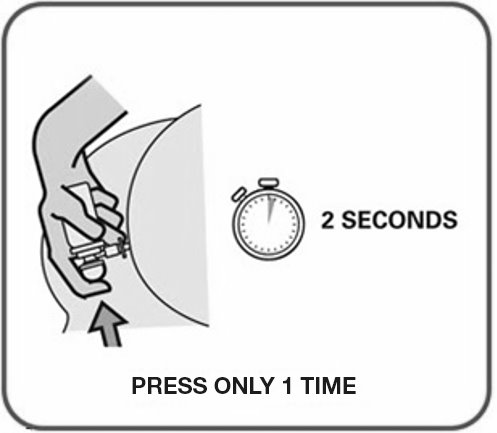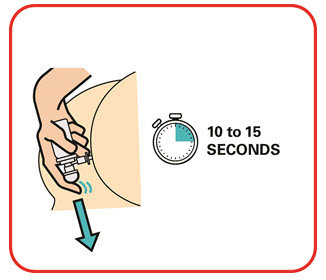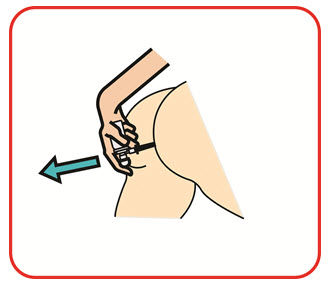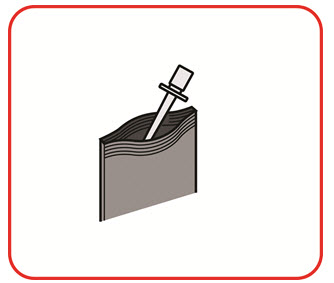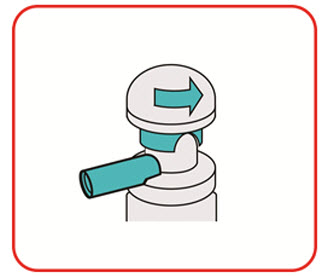 DRUG LABEL: budesonide
NDC: 68682-658 | Form: AEROSOL, FOAM
Manufacturer: Oceanside Pharmaceuticals
Category: prescription | Type: HUMAN PRESCRIPTION DRUG LABEL
Date: 20211001

ACTIVE INGREDIENTS: BUDESONIDE 2 mg/1 1
INACTIVE INGREDIENTS: CETYL ALCOHOL; CITRIC ACID MONOHYDRATE; EDETATE DISODIUM; CETOSTEARYL ALCOHOL; POLYSORBATE 60; STEARETH-10; PROPYLENE GLYCOL; WATER; BUTANE; PROPANE; ISOBUTANE

HIGHLIGHTS OF PRESCRIBING INFORMATION

These highlights do not include all the information needed to use BUDESONIDE RECTAL FOAM safely and effectively. See full prescribing information for BUDESONIDE RECTAL FOAM.
BUDESONIDE rectal foam
Initial U.S. Approval: 1997

1 INDICATIONS AND USAGE

Budesonide rectal foam is a glucocorticosteroid indicated for the induction of remission in patients with active mild to moderate distal ulcerative colitis extending up to 40 cm from the anal verge. (1)

2 DOSAGE AND ADMINISTRATION

- The recommended dosage is 1 metered dose administered twice daily for 2 weeks followed by 1 metered dose administered once daily for 4 weeks. (2.1)
- For rectal administration only. (2.2)
- Warm the canister in the hands while shaking it vigorously for 10 to 15 seconds prior to use. (2.2)

3 DOSAGE FORMS AND STRENGTHS

Budesonide rectal foam contains 2 mg budesonide per metered dose. (3)

4 CONTRAINDICATIONS

Known hypersensitivity to budesonide or any of the ingredients in budesonide rectal foam. (4)

5 WARNINGS AND PRECAUTIONS

- Hypercorticism and adrenal suppression: Follow general warnings concerning glucocorticosteroids. (5.1)
- Impaired Adrenal Function in Patients Transferred from Other Glucocorticoids: Taper slowly from glucocorticosteroids with high systemic effects; monitor for withdrawal symptoms and unmasking of allergies (rhinitis, eczema). (5.2)
- Increased Risk of Infection, including serious and fatal chicken pox and measles: Monitor patients with active or quiescent tuberculosis infection, untreated fungal, bacterial, systemic viral or parasitic infections, or ocular herpes simplex. (5.3)
- Other Glucocorticosteroid Effects: Monitor patients with other conditions where glucocorticoids may have unwanted effects. (5.4)
- Flammable Contents: The contents of budesonide rectal foam are flammable. Instruct the patient to avoid fire, flame and smoking during and immediately following administration. (5.5)

6 ADVERSE REACTIONS

Most common adverse reactions (≥ 2%) are decreased blood cortisol, adrenal insufficiency, and nausea. (6.1)

To report SUSPECTED ADVERSE REACTIONS, contact Oceanside Pharmaceuticals at 1-800-321-4576 or FDA at 1-800-FDA-1088 or www.fda.gov/medwatch.

7 DRUG INTERACTIONS

CYP3A4 Inhibitors (e.g., ketoconazole, grapefruit juice): May cause increased systemic corticosteroid effects; avoid concomitant use. (7.1)

8 USE IN SPECIFIC POPULATIONS

- Pregnancy: Based on animal data, may cause fetal harm. (8.1)
- Hepatic Impairment: Monitor patients for signs and/or symptoms of hypercorticism. (8.6)

FULL PRESCRIBING INFORMATION

1 INDICATIONS AND USAGE

Budesonide rectal foam is indicated for the induction of remission in patients with active mild to moderate distal ulcerative colitis extending up to 40 cm from the anal verge.

2 DOSAGE AND ADMINISTRATION

2.1 Recommended Dosage

The recommended dosage regimen is 1 metered dose administered rectally twice daily for 2 weeks followed by 1 metered dose administered rectally once daily for 4 weeks.

2.2 Administration Instructions

Advise patients:

- Budesonide rectal foam is only to be applied rectally. It is not for oral use.
- Before using budesonide rectal foam, use the bathroom to empty your bowels.
- Each applicator is coated with a lubricant. If additional lubrication is needed, petrolatum or petroleum jelly can also be used.
- Warm the canister in the hands while shaking it vigorously for 10 to 15 seconds prior to use.
- Budesonide rectal foam can be used in a standing, lying or sitting position (e.g., while using the toilet).
- Apply budesonide rectal foam in the morning and the evening for the first 2 weeks of treatment; then once daily in the evening for the next 4 weeks. When applied in the evening, use immediately prior to bedtime. Try not to empty your bowels again until the next morning.
- Avoid concomitant use of CYP3A4 inhibitors (e.g., ketoconazole, grapefruit juice) during treatment with budesonide rectal foam.

3 DOSAGE FORMS AND STRENGTHS

Budesonide rectal foam is formulated as an emulsion which is filled into an aluminum canister with an aerosol propellant. It is available in 1 strength: 2 mg budesonide per metered dose.

4 CONTRAINDICATIONS

Budesonide rectal foam is contraindicated in patients with a history of a known hypersensitivity to budesonide or any of the ingredients of budesonide rectal foam. Reactions have included anaphylaxis [see Adverse Reactions (6.2)].

5 WARNINGS AND PRECAUTIONS

5.1 Hypercorticism and Adrenal Axis Suppression

When glucocorticosteroids are used chronically, systemic effects such as hypercorticism and adrenal suppression may occur. Glucocorticosteroids can reduce the response of the hypothalamus-pituitary-adrenal (HPA) axis to stress. In situations where patients are subject to surgery or other stress situations, supplementation with a systemic glucocorticosteroid is recommended. Since budesonide rectal foam contains a glucocorticosteroid, general warnings concerning glucocorticoids should be followed [see Clinical Pharmacology (12.2)].

Reduced liver function affects the elimination of glucocorticosteroids, and increased systemic availability of oral budesonide has been demonstrated in patients with liver cirrhosis [see Use in Specific Populations (8.6)].

5.2 Impaired Adrenal Suppression in Patients Transferred from Other Glucocorticoids

Monitor patients who are transferred from glucocorticosteroid treatment with higher systemic effects to glucocorticosteroids with lower systemic effects, such as budesonide rectal foam, since symptoms attributed to withdrawal of steroid therapy, including those of acute adrenal suppression or benign intracranial hypertension, may develop. Adrenocortical function monitoring may be required in these patients and the dose of glucocorticosteroid treatment with high systemic effects should be reduced cautiously.

Replacement of systemic glucocorticosteroids with budesonide rectal foam may unmask allergies (e.g., rhinitis and eczema), which were previously controlled by the systemic drug.

5.3 Increased Risk of Infection

Patients who are on drugs that suppress the immune system are more susceptible to infection than healthy individuals. Chicken pox and measles, for example, can have a more serious or even fatal course in susceptible patients or patients on immunosuppressant doses of glucocorticosteroids. In patients who have not had these diseases, particular care should be taken to avoid exposure.

How the dose, route and duration of glucocorticosteroid administration affect the risk of developing a disseminated infection is not known. The contribution of the underlying disease and/or prior glucocorticosteroid treatment to the risk is also not known. If exposed, therapy with varicella zoster immune globulin (VZIG) or pooled intravenous immunoglobulin (IVIG), as appropriate, may be indicated. If exposed to measles, prophylaxis with pooled intramuscular immunoglobulin (IG) may be indicated (see prescribing information for VZIG and IG). If chicken pox develops, treatment with antiviral agents may be considered.

Glucocorticosteroids should be used with caution, if at all, in patients with active or quiescent tuberculosis infection, untreated fungal, bacterial, systemic viral or parasitic infections, or ocular herpes simplex.

5.4 Other Glucocorticosteroid Effects

Monitor patients with hypertension, diabetes mellitus, osteoporosis, peptic ulcer, glaucoma or cataracts, or with a family history of diabetes or glaucoma, or with any other condition where glucocorticosteroids may have unwanted effects.

5.5 Flammable Contents

The contents of budesonide rectal foam include n-butane, isobutane and propane as propellants which are flammable. Instruct the patient to avoid fire, flame, and smoking during and immediately following administration. Patients should temporarily discontinue use of budesonide rectal foam before initiation of bowel preparation for colonoscopy and consult their healthcare provider before resuming therapy.

6 ADVERSE REACTIONS

Serious and important adverse reactions include:

- Hypercorticism and adrenal axis suppression [see Warnings and Precautions (5.1)]
- Symptoms of steroid withdrawal in those patients transferring from systemic glucocorticosteroid therapy [see Warnings and Precautions (5.2)]
- Increased susceptibility to infection [see Warnings and Precautions (5.3)]
- Other glucocorticosteroid effects [see Warnings and Precautions (5.4)]

6.1 Clinical Trials Experience

Because clinical trials are conducted under widely varying conditions, adverse reaction rates observed in the clinical trials of a drug cannot be directly compared with rates in the clinical trials of another drug and may not reflect the rates observed in practice.

The data described below reflect exposure to budesonide rectal foam in 332 patients with active mild to moderate distal ulcerative colitis extending up to 40 cm from the anal verge. The median duration of exposure was 42 days. This included 14 patients exposed for at least 6 months.

Budesonide rectal foam was studied primarily in 2 placebo-controlled, 6-week trials in patients with active disease (Study 1 and Study 2). In these trials, 268 patients received budesonide rectal foam 2 mg twice a day for 2 weeks followed by 2 mg once a day for 4 weeks [see Clinical Studies (14)].

The most common adverse reactions (≥ 2% of the budesonide rectal foam or Placebo group and at higher frequency in the budesonide rectal foam group) were decreased blood cortisol, adrenal insufficiency, and nausea (Table 1). Decreased blood cortisol was defined as a morning cortisol level of <5 mcg/dL. Adrenal insufficiency was defined as a cortisol level of <18 mcg/dL at 30 minutes post-challenge with adrenocorticotropic hormone (ACTH).

A total of 10% of budesonide rectal foam-treated patients discontinued treatment due to an adverse reaction compared with 4% of placebo-treated patients.

Table 1: Summary of Adverse Reactions in 2 Placebo-Controlled Trials [Experienced by ≥ 2% of the budesonide rectal foam or Placebo group and at higher frequency in the budesonide rectal foam group.] (Studies 1 and 2)
Adverse Reaction | Budesonide Rectal Foam 2 mg/25 mL N=268 n (%) | Placebo N=278 n (%)
Decreased blood cortisol [Decreased blood cortisol was defined as a morning cortisol level of <5 mcg/dL.] | 46 (17) | 6 (2)
Adrenal insufficiency [Adrenal insufficiency was defined as a cortisol level of <18 mcg/dL at 30 minutes post-challenge with ACTH.] | 10 (4) | 2 (1)
Nausea | 6 (2) | 2 (1)

Of the 46 budesonide rectal foam treated patients with decreased blood cortisol (defined as a morning cortisol level of <5 mcg/dL) reported as an adverse event, none had adrenal insufficiency (defined as a cortisol level of <18 mcg/dL at 30 minutes post-challenge with ACTH) (see Table 2). All cases of adrenal insufficiency resolved.

Table 2 summarizes the percentages of patients reporting glucocorticoid related effects in the 2 placebo-controlled trials (Studies 1 and 2).

Table 2: Summary of Glucocorticoid Related Effects in Two Placebo-Controlled Trials (Studies 1 and 2)
Adverse Reaction | Budesonide Rectal Foam 2 mg/25 mL N=268 n (%) | Placebo N=278 n (%)
Overall | 60 (22) | 10 (4)
Blood cortisol decreased | 46 (17) [Decreases in serum cortisol levels associated with budesonide treatment were seen at Weeks 1 and 2 (twice daily treatment) in the budesonide rectal foam group, but gradually returned to baseline levels during the 4 weeks of once daily treatment.] | 6 (2)
Adrenal insufficiency | 10 (4) | 2 (1)
Insomnia | 1 (0.4) | 1 (0.4)
Sleep disorder | 1 (0.4) | 0
Acne | 1 (0.4) | 0
Depression | 1 (0.4) | 1 (0.4)
Hyperglycemia | 1 (0.4) | 0

No clinically significant differences were observed with respect to the overall percentages of patients with any glucocorticoid related effects between budesonide rectal foam and placebo after 6 weeks of therapy.

For additional details on morning cortisol levels and the response to the ACTH stimulation test, see Clinical Pharmacology (12.2).

6.2 Postmarketing Experience

In addition to adverse reactions reported from clinical trials for budesonide rectal foam, the following adverse reactions have been identified during post-approval use of other oral and rectal formulations of budesonide. Because these reactions are reported voluntarily from a population of uncertain size, it is not always possible to reliably estimate their frequency or establish a causal relationship to drug exposure.

Cardiac disorders: hypertension

Gastrointestinal disorders: pancreatitis

General disorders and administration site conditions: pyrexia, peripheral edema

Immune system disorders: anaphylactic reactions

Nervous system disorders: dizziness, benign intracranial hypertension

Psychiatric disorders: mood swings

Skin and subcutaneous tissue disorders: pruritus, maculopapular rash, allergic dermatitis

7 DRUG INTERACTIONS

7.1 CYP3A4 Inhibitors

The active ingredient of budesonide rectal foam, budesonide, is metabolized by CYP3A4. Inhibitors of CYP3A4 activity (such as ketoconazole, itraconazole, ritonavir, indinavir, saquinavir, erythromycin, cyclosporine and grapefruit juice) can increase systemic budesonide concentrations. Avoid concomitant use of CYP3A4 inhibitors with budesonide rectal foam [see Clinical Pharmacology (12.3)].

8 USE IN SPECIFIC POPULATIONS

8.1 Pregnancy

Risk Summary

Limited published studies report on the use of budesonide in pregnant women; however, the data are insufficient to inform a drug-associated risk for major birth defects and miscarriage. There are clinical considerations (see Clinical Considerations). In animal reproduction studies with pregnant rats and rabbits, subcutaneous administration of budesonide during organogenesis at doses 1.2 times and 0.12 times, respectively, the human intrarectal dose of 4 mg/day, resulted in increased fetal loss, decreased pup weights, and skeletal abnormalities. Maternal toxicity was observed in both rats and rabbits at these dose levels (see Data). Based on animal data, advise pregnant women of the potential risk to a fetus.

The estimated background risk of major birth defects and miscarriage of the indicated population is unknown. All pregnancies have a background risk of birth defect, loss, or other adverse outcomes. In the U.S. general population, the estimated background risk of major birth defects and miscarriage in clinically recognized pregnancies is of 2% to 4%, and 15% to 20%, respectively.

Clinical Considerations

Disease-Associated Maternal and/or Embryo/Fetal Risk

Published data suggest that increased disease activity is associated with the risk of developing adverse pregnancy outcomes in women with ulcerative colitis. Adverse pregnancy outcomes include preterm delivery (before 37 weeks of gestation), low birth weight (less than 2500 g) infants, and small for gestational age at birth.

Fetal/Neonatal Adverse Reactions

Hypoadrenalism may occur in infants born of mothers receiving corticosteroids during pregnancy. Infants should be carefully observed for signs of hypoadrenalism, such as poor feeding, irritability, weakness, and vomiting, and managed accordingly [see Warnings and Precautions (5.1)].

Data

Animal Data

Budesonide was teratogenic and embryolethal in rabbits and rats.

In an embryo-fetal development study in pregnant rats dosed subcutaneously with budesonide during the period of organogenesis from gestation days 6-15 there were effects on fetal development and survival at subcutaneous doses up to approximately 500 mcg/kg in rats (approximately 1.2 times the recommended human intrarectal dose on a body surface area basis). In an embryo-fetal development study in pregnant rabbits dosed during the period of organogenesis from gestation days 6-18, there was an increase in maternal abortion, and effects on fetal development and reduction in litter weights at subcutaneous doses up to approximately 25 mcg/kg in rabbits (approximately 0.12 times the recommended human intrarectal dose of 4 mg/day on a body surface area basis). Maternal toxicity, including reduction in body weight gain, was observed at subcutaneous doses of 5 mcg/kg in rabbits (approximately 0.02 times the recommended human intrarectal dose on a body surface area basis) and 500 mcg/kg in rats (approximately 1.2 times the recommended human intrarectal dose of 4 mg/day on a body surface area basis).

In a pre-and post-natal development study, rats dosed subcutaneously with budesonide during the period of Day 15 post coitum to Day 21 postpartum, budesonide had no effects on delivery but did have an effect on growth and development of offspring. In addition, offspring survival was reduced, and surviving offspring had decreased mean body weights at birth and during lactation at exposures 0.05 times the MRHD (on a mg/m^2 basis at maternal subcutaneous doses of 20 mcg/kg/day and higher). These findings occurred in the presence of maternal toxicity.

8.2 Lactation

Risk Summary

Lactation studies have not been conducted with budesonide rectal foam or other rectally administered budesonide products and no information is available on the effects of budesonide on the breastfed infant or the effects of the drug on milk production. One published study reports that budesonide is present in human milk following maternal inhalation of budesonide (see Data). The developmental and health benefits of breastfeeding should be considered along with the mother’s clinical need for budesonide rectal foam and any potential adverse effects on the breastfed child from budesonide rectal foam or from the underlying maternal condition. Data

One published study reports that budesonide is present in human milk following maternal inhalation of budesonide and the milk/plasma ratio ranged between 0.4 and 0.5. Budesonide plasma concentrations were not detected, and no adverse events were noted in the breastfed infants following maternal use of inhaled budesonide. The systemic exposure (AUC0-12) following administration of 400 mcg twice a day of inhaled budesonide ranged from 1.27 to 2.26 ng*hr/mL. The estimated budesonide AUC0-12 following rectal administration of 2 mg twice a day budesonide was 4.31 ng*hr/mL [see Clinical Pharmacology (12.3)]. Budesonide exposure to the nursing child may be higher with maternal rectal administration of budesonide than with maternal inhaled administration of budesonide.

8.4 Pediatric Use

The safety and effectiveness of budesonide rectal foam has not been established in pediatric patients.

Children who are treated with corticosteroids by any route may experience a decrease in their growth velocity. This negative impact of corticosteroids on growth has been in the absence of laboratory evidence of hypothalamic-pituitary-adrenal (HPA) axis suppression. The long-term effects of this reduction in growth velocity associated with corticosteroid treatment, including the impact on final adult height, are unknown. Growth velocity may therefore be a more sensitive indicator of systemic corticosteroid exposure in children than some commonly used tests of HPA axis function. The linear growth of children treated with corticosteroids by any route should be monitored (e.g., via stadiometry), and the potential growth effects of prolonged treatment should be weighed against clinical benefits obtained and the availability of other treatment alternatives. In order to minimize the potential growth effects of corticosteroids, children should be titrated to the lowest effective dose.

8.5 Geriatric Use

Clinical studies with budesonide rectal foam did not include sufficient numbers of patients aged 65 and over to determine whether they respond differently than younger patients. Other reported clinical experience has not identified differences in responses between the elderly and younger patients. In general, dose selection for an elderly patient should be cautious, usually starting at the low end of the dosing range, reflecting the greater frequency of decreased hepatic, renal, or cardiac function, and of concomitant disease or other drug therapy.

8.6 Hepatic Impairment

No dosage adjustment is needed for patients with mild (Child-Pugh Class A) hepatic impairment. Patients with moderate to severe hepatic impairment (Child-Pugh Class B or C) should be monitored for increased signs and/or symptoms of hypercorticism. Discontinuing the use of budesonide rectal foam should be considered in these patients if signs of hypercorticism are observed [see Warnings and Precautions (5.1) andClinical Pharmacology (12.3)].

10 OVERDOSAGE

Acute overdosage with budesonide rectal foam is unlikely. However, budesonide rectal foam is absorbed systemically and chronic overdosage may result in signs/symptoms of hypercorticism [see Warnings and Precautions (5.1)].

11 DESCRIPTION

Budesonide rectal foam contains budesonide, a non-halogenated synthetic glucocorticoid, as the active ingredient. It is a mixture of the 2 epimers (22R and 22S) differing in the position of an acetal chain. Both epimers are active glucocorticoids applied in a mixture of approximately 1:1.

Budesonide is designated chemically as (RS)-11β, 16α, 17,21 tetrahydroxypregna-1,4-diene-3,20-dione cyclic 16,17-acetal with butyraldehyde. The empirical formula of budesonide is C25H34O6 and its molecular weight is 430.5. Its structural formula is:

Budesonide rectal foam contains 2 mg budesonide per metered dose.

Inactive ingredients: cetyl alcohol, citric acid monohydrate, edetate disodium, emulsifying wax, polyoxyl (10) stearyl ether, propylene glycol, and purified water.

Propellant: n-butane, isobutane, and propane.

12 CLINICAL PHARMACOLOGY

12.1 Mechanism of Action

Budesonide has glucocorticosteroid (GCS) activity.

12.2 Pharmacodynamics

Treatment with glucocorticosteroids, including budesonide rectal foam, is associated with a suppression of endogenous cortisol concentrations and an impairment of the hypothalamic-pituitary-adrenal (HPA) axis function. These effects were measured by determination of plasma cortisol concentrations and responses to adrenocorticotropin challenge (i.e., ACTH stimulation test) in 2 placebo-controlled, 6-week trials in patients with active disease [see Clinical Studies (14)]. These trials enrolled subjects with post-ACTH stimulation cortisol levels of >18 mcg/dL at baseline. Subjects received budesonide rectal foam 2 mg or a placebo twice daily for 2 weeks followed by once daily for 4 weeks. Normal morning serum cortisol levels >5 mcg/dL were maintained in 85% and 84% of budesonide rectal foam treated subjects during Weeks 1 and 2 (twice daily treatment) and 93% and 94% during Weeks 4 and 6 (once daily treatment), respectively (see Table 3).

At baseline (predose), 84% of subjects in the budesonide rectal foam group had a normal response to the ACTH challenge and at Week 6, 63% of subjects had a normal response to the ACTH challenge; in the placebo group, these values were 86% and 76%, respectively (see Table 3). ACTH stimulation test was not performed routinely during the twice daily treatment period (Weeks 1 and 2).

Table 3: Proportion of Subjects with Normal Endogenous Cortisol Levels (>5 mcg/dL) During the Study and Proportion of Subjects with Normal Response to ACTH Challenge
Cortisol Parameter | Budesonide Rectal Foam 2 mg/25 mL N=268 n (%) |  | Placebo N=278 n (%)
Total cortisol ˃5 mcg/dL
(lower limit of normal range)
Baseline | 259/268 | (96.6) | 275/278 | (98.9)
Week 1 | 224/263 | (85.2) | 264/269 | (98.1)
Week 2 | 216/257 | (84.0) | 263/266 | (98.9)
Week 4 | 218/235 | (92.8) | 243/249 | (97.6)
Week 6 | 211/224 | (94.2) | 234/241 | (97.1)
Normal response to ACTH challenge [The normal response to ACTH challenge included 3 criteria, as defined in the cosyntropin label: 1) morning cortisol level >5 mcg/dL; 2) increase in cortisol level by ≥7 mcg/dL above the morning (pre-challenge) level following ACTH challenge; and cortisol level of >18 mcg/dL following ACTH challenge.]
Baseline | 222/266 | (83.5) | 238/278 | (85.6)
Week 6 [Denominator includes 20 subjects in the budesonide rectal foam arm and 2 subjects in the placebo arm who discontinued prior to Week 6 due to adverse events related to low cortisol or abnormal response to ACTH challenge.] | 148/236 | (62.7) | 180/237 | (75.9)

12.3 Pharmacokinetics

Absorption

Distal Ulcerative Colitis Patients

Based on population pharmacokinetic analysis from sparse PK samples from phase 3 studies, the estimated AUC0-12 following administration of budesonide rectal foam 2 mg twice a day was 4.31 ng*hr/mL with a CV of 64% in the target patient population.

Distribution

The volume of distribution (VSS) of budesonide varies between 2.2 and 3.9 L/kg in healthy subjects and in patients. Plasma protein binding is estimated to be 85 to 90% in the concentration range of 1 to 230 nmol/L, independent of gender. The erythrocyte/plasma partition ratio at clinically relevant concentrations is approximately 0.8.

Elimination

Metabolism

Following absorption, budesonide is subject to first-pass metabolism. In vitro experiments in human liver microsomes demonstrate that budesonide is rapidly and extensively biotransformed, mainly by CYP3A4, to its 2 major metabolites, 6β-hydroxy budesonide and 16α-hydroxy prednisolone. The glucocorticoid activity of these metabolites is negligible (<1/100) in relation to that of the parent compound.

In vivo investigations with intravenous doses in healthy subjects demonstrate that budesonide has a plasma clearance of 0.9-1.8 L/min. These plasma clearance values approach the estimated liver blood flow, suggesting that budesonide is a high hepatic clearance drug.

Excretion

Budesonide is excreted in urine and feces in the form of metabolites. After oral as well as intravenous administration of micronized [^3H]-budesonide, approximately 60% of the recovered radioactivity is found in urine. The major metabolites, including 6β-hydroxybudesonide and 16α-hydroxyprednisolone, are mainly renally excreted, intact or in conjugated forms. No unchanged budesonide is detected in urine.

Specific Populations

Patients with Renal Impairment

The pharmacokinetics of budesonide in patients with renal impairment has not been studied. Intact budesonide is not renally excreted, but metabolites are to a large extent, and might therefore reach higher levels in patients with impaired renal function. However, these metabolites have negligible corticosteroid activity as compared with budesonide.

Patients with Hepatic Impairment

The effect of hepatic impairment on the pharmacokinetics of budesonide rectal foam has not been studied. In a study in patients with mild to moderate hepatic impairment (Child-Pugh Class A and Child-Pugh Class B) dosed with budesonide 4 mg oral capsules, systemic exposure was similar between patients with mild hepatic impairment (Child-Pugh Class A; n=4) and healthy subjects (n=8), and 3.5-fold higher in patients with moderate hepatic impairment (Child-Pugh Class B; n=4) than in healthy subjects. For the intravenous dose, no significant differences in CL or VSS are observed. Patients with severe liver dysfunction (Child-Pugh Class C) were not studied [see Use in Specific Populations (8.6)].

Drug Interaction Studies

Budesonide is metabolized via CYP3A4. Potent inhibitors of CYP3A4 can increase the plasma concentrations of budesonide. Co-administration of ketoconazole (inhibitor of CYP3A4) results in an 8-fold increase in AUC of oral budesonide, compared to budesonide alone. Grapefruit juice, an inhibitor of gut mucosal CYP3A, approximately doubles the systemic exposure of oral budesonide. Conversely, induction of CYP3A4 can result in the lowering of budesonide plasma concentrations. The effect of CYP3A4 inhibitors and inducers on the pharmacokinetics of budesonide rectal foam have not been studied [see Dosage and Administration (2) and Drug Interactions (7)].

Oral contraceptives containing ethinyl estradiol, which are also metabolized by CYP3A4, do not affect the pharmacokinetics of oral budesonide. Budesonide does not affect the plasma concentrations of oral contraceptives (i.e., ethinyl estradiol).

In vitro interaction studies performed with budesonide showed that budesonide did not inhibit human cytochrome P450 isoenzymes CYP1A2, CYP2B6, CYP2C9, CYP2D6, or CYP2E1 at concentrations ranging from 0.11 to 1130 ng/mL. Isoenzyme CYP3A4 was inhibited at the highest concentration tested but the IC50 was >1130 ng/mL. Budesonide rectal foam is not expected to inhibit these enzymes in clinical use. No significant induction of CYP1A2, CYP2B6, CYP2C9 or CYP3A4/5 expression was observed in human hepatocytes in vitro at budesonide concentrations up to 9000 nM (3.88 mcg/mL).

In an in vitro study, budesonide was not a substrate of human transporters OATP1B3 and may be a weak substrate of OATP1B1. Budesonide at concentrations up to 300 nM (129 ng/mL) did not inhibit OATP1B1 or OATP1B3.

Budesonide was not a substrate of BCRP and was a weak substrate of P-glycoprotein. Budesonide was a weak inhibitor of P-glycoprotein (IC50 9.78 µM or 4.21 mcg/mL) and BCRP (IC50 43.1 µM or 18.6 mcg/mL). Budesonide rectal foam is not expected to inhibit these transporters in clinical use.

13 NONCLINICAL TOXICOLOGY

13.1 Carcinogenesis, Mutagenesis, Impairment of Fertility

Carcinogenicity

Carcinogenicity studies with budesonide were conducted in rats and mice. In a 2-year study in Sprague-Dawley rats, budesonide caused a statistically significant increase in the incidence of gliomas in male rats at an oral dose of 50 mcg/kg (approximately 0.12 times the recommended intrarectal dose of 4 mg/day in humans, based on the body surface area). In addition, there were increased incidences of primary hepatocellular tumors in male rats at 25 mcg/kg (approximately 0.06 times the recommended intrarectal dose of 4 mg/day in humans, based on the body surface area) and above. No tumorigenicity was seen in female rats at oral doses up to 50 mcg/kg (approximately 0.12 times the recommended intrarectal dose of 4 mg/day in humans, based on the body surface area).

In an additional 2-year study in male Sprague-Dawley rats, budesonide caused no gliomas at an oral dose of 50 mcg/kg (approximately 0.12 times the recommended intrarectal dose of 4 mg/day in humans, based on the body surface area). However, it caused a statistically significant increase in the incidence of hepatocellular tumors at an oral dose of 50 mcg/kg (approximately 0.12 times the recommended intrarectal dose of 4 mg/day in humans, based on the body surface area). The concurrent reference glucocorticosteroids (prednisolone and triamcinolone acetonide) showed similar findings. In a 91-week study in mice, budesonide caused no treatment-related carcinogenicity at oral doses up to 200 mcg/kg (approximately 0.24 times the recommended intrarectal dose of 4 mg/day in humans, based on the body surface area).

Mutagenesis

Budesonide showed no evidence of mutagenic potential in the Ames test, the mouse lymphoma cell forward gene mutation (TK+/-) test, the human lymphocyte chromosome aberration test, the Drosophila melanogaster sex-linked recessive lethality test, the rat hepatocyte UDS test or the mouse micronucleus test.

Impairment of Fertility

In rats, budesonide had no effect on fertility at subcutaneous doses up to 80 mcg/kg (approximately 0.20 times recommended intrarectal dose of 4 mg/day in humans, based on the body surface area). However, it caused a decrease in prenatal viability and viability in pups at birth and during lactation, along with a decrease in maternal body-weight gain, at subcutaneous doses of 20 mcg/kg (approximately 0.05 times recommended intrarectal dose of 4 mg/day in humans, based on the body surface area) and above. No such effects were noted at 5 mcg/kg.

14 CLINICAL STUDIES

The safety and efficacy of budesonide rectal foam were evaluated in 2 replicate, randomized, double-blind, placebo-controlled, multi-center trials (Studies 1 and 2).

Participants in the trials were adult patients with active mild-to-moderate distal ulcerative colitis with disease extending at least 5 cm but no further than 40 cm from the anal verge (confirmed by endoscopy). To be eligible, patients had to have a Modified Mayo Disease Activity Index (MMDAI) score between 5 and 10, inclusive, a rectal bleeding subscore of 2 or 3, and an endoscopy subscore of 2 or 3. The MMDAI score ranges from 0 to 12 and has 4 subscales that are each scored from 0 (normal) to 3 (most severe): stool frequency, rectal bleeding, findings on endoscopy, and physician global assessment. An endoscopy subscore of 2 is defined by marked erythema, lack of vascular pattern, friability, and erosions; an endoscopy subscore of 3 is defined by spontaneous bleeding and ulceration.

Oral and rectal corticosteroids, and rectal 5-aminosalicylic acid (5-ASA) products were prohibited during the course of the trials but were allowed as rescue therapy. Oral 5-ASA products were allowed at doses ≤ 4.8 grams/day.

In total, 546 subjects were randomized in these trials: 267 subjects to budesonide rectal foam and 279 subjects to placebo. In each trial (Study 1 and Study 2), patients received budesonide rectal foam 2 mg or placebo twice daily for 2 weeks followed by once daily for 4 weeks.

The median age was 41 years and 42 years, 5% and 8% were ≥ 65 years of age, and 43% and 45% were male, in Studies 1 and 2, respectively. In each of these trials, 90% were Caucasian, 7-8% were African American, and 3% were Asian or Other.

The majority of patients had a baseline diagnosis of proctosigmoiditis (69% and 74%) in Studies 1 and 2, respectively. The remaining patients had a baseline diagnosis of proctitis. Concomitant oral 5-ASA use at baseline was 59% and 51% in Studies 1 and 2, respectively.

Baseline MMDAI total score was 7.8 and 7.9 in the budesonide rectal foam group and placebo group, respectively, of Study 1; and 7.9 and 8.0 in the budesonide rectal foam group and placebo group, respectively, of Study 2. The mean stool frequency subscore at baseline was 1.8 and 1.9 in the budesonide rectal foam group and placebo group, respectively, of Study 1; and 1.7 and 1.8 in the budesonide rectal foam group and placebo group, respectively, of Study 2.

In each trial (Study 1 and Study 2), the primary endpoint was the proportion of subjects who were in remission after 6 weeks of treatment. Remission was defined as a decrease or no change in the stool frequency subscore from baseline, a rectal bleeding subscore of 0, and an endoscopy score of 0 or 1. (An endoscopy subscore of zero is defined by normal or inactive disease; an endoscopy subscore of 1 is defined by erythema and decreased vascular pattern.)

In each trial (Study 1 and Study 2), a higher proportion of patients in the budesonide rectal foam group than in the placebo group were in remission at Week 6 and had a rectal bleeding subscore of 0 at Week 6 (Table 4).

Table 4: Efficacy Results: Studies 1 and 2
 | Study 1
Efficacy Endpoint | Budesonide Rectal Foam N=133 | Placebo N=132 | p-value [p-values obtained from the Cochran-Mantel-Haenszel (CMH) test.] | Treatment Difference (95% CI)
Remission at Week 6 [Remission was defined as an endoscopy subscore of 0 or 1, a rectal bleeding subscore of 0, and a decrease or no change in stool frequency subscore from baseline.] | 38.3% | 25.8% | 0.032 | 12.6% (1.5%, 23.7%)
Rectal Bleeding subscore = 0 at Week 6 | 46.6% | 28.0% | 0.002 | 18.6% (7.2%, 30%)
Study 2
 | Budesonide Rectal Foam N=134 | Placebo N=147 | p-value | Treatment Difference (95% CI)
Remission at Week 6 | 44.0% | 22.4% | <0.001 | 21.6% (10.8%, 32.4%)
Rectal Bleeding subscore = 0 at Week 6 | 50.0% | 28.6% | <0.001 | 21.4% (10.3%, 32.6%)

CI: Confidence Interval

In Study 1, the percentage of patients with endoscopy subscore of 0 or 1 at Week 6 was 55.6% in the budesonide rectal foam group versus 43.2% in the placebo group. In Study 2, the percentage of patients with endoscopy subscore of 0 or 1 at Week 6 was 56.0% in the budesonide rectal foam group versus 36.7% in the placebo group (an endoscopy subscore of 0 is defined by normal or inactive disease; an endoscopy subscore of 1 is defined by erythema and decreased vascular pattern).

In patients that met the primary endpoint of remission in Study 1, the mean (SD) decrease in stool frequency subscore was 1.2 (0.9) in the budesonide rectal foam group and 1.2 (0.8) in the placebo group. In patients that met the primary endpoint of remission in Study 2, the mean (SD) decrease in stool frequency subscore was 1.3 (0.8) in the budesonide rectal foam group and 1.1 (0.9) in the placebo group.

16 HOW SUPPLIED/STORAGE AND HANDLING

Budesonide rectal foam is supplied as a kit containing 2 aerosol canisters with 28 PVC applicators coated with paraffin lubricant for administration of the foam (NDC 68682-658-03). Each canister (NDC 68682-658-02) is labeled with a net weight of 33.4 g and contains 14 metered doses.

Storage

Store at 20° to 25°C (68° to 77°F); excursions permitted to 15° to 30°C (59° to 86°F) [see USP Controlled Room Temperature].

Handling

Budesonide rectal foam contains a flammable propellant. Do not have the canister burned after use and do not spray contents directly towards flames.

- Do not expose to heat or store at temperatures above 120°F (49°C).
- Flammable. Avoid fire, flame, or smoking during and immediately following administration.
- Contents under pressure. Do not puncture or incinerate.

DO NOT REFRIGERATE.

17 PATIENT COUNSELING INFORMATION

Advise the patient to read the FDA-approved patient labeling (PATIENT INFORMATION and INSTRUCTIONS FOR USE).

Administration

Advise patients:

- Budesonide rectal foam is only to be applied rectally. It is not for oral use.
- Before using budesonide rectal foam, use the bathroom to empty your bowels.
- Each applicator is coated with a lubricant. If additional lubrication is needed, petrolatum or petroleum jelly can also be used.
- Warm the canister in the hands while shaking it vigorously for 10 to 15 seconds prior to use.
- Budesonide rectal foam can be used in a standing, lying or sitting position (e.g., while using the toilet).
- Apply budesonide rectal foam in the morning and the evening for the first 2 weeks of treatment; then once daily in the evening for the next 4 weeks. When applied in the evening, use immediately prior to bedtime. Try not to empty your bowels again until the next morning.
- Avoid consumption of grapefruit or grapefruit juice during treatment with budesonide rectal foam.
- Avoid fire, flame, and smoking during and immediately following administration since budesonide rectal foam is flammable.

Hypercorticism and Adrenal Suppression

Advise patients that budesonide rectal foam may cause hypercorticism and adrenal suppression and that they should taper slowly from systemic corticosteroids if transferring to budesonide rectal foam [see Warnings and Precautions (5.1), (5.2)]. Advise patients that replacement of systemic glucocorticosteroids with budesonide rectal foam may unmask allergies (e.g., rhinitis and eczema), which were previously controlled by the systemic drug.

Increased Risk of Infection

Advise patients to avoid exposure to people with chicken pox or measles and if exposed, consult a physician. Also, inform patients that they are at increased risk of developing a variety of infections, including worsening of existing tuberculosis, fungal, bacterial, viral, or parasitic infections, or ocular herpes simplex and to contact their physician if they develop any symptoms of infection [see Warnings and Precautions (5.3)].

Pregnancy

Advise female patients that budesonide rectal foam may cause fetal harm and to inform their healthcare provider with a known or suspected pregnancy [see Use in Specific Populations (8.1)].

Distributed by:

Oceanside Pharmaceuticals, a division of

Bausch Health US, LLC

Bridgewater, NJ 08807 USA

Manufactured by:

ASM Aerosol-Service AG

Industriestrasse 11

CH-4313 Möhlin Switzerland

Product marketed and distributed under license from Dr. Falk Pharma.

© 2021 Bausch Health Companies Inc. or its affiliates

9767800 EX00245

Patient Information

Budesonide rectal foam

What is budesoniderectal foam?

Budesonide rectal foam is a prescription corticosteroid medicine used to help get mild to moderate active ulcerative colitis that extends from the rectum to the sigmoid colon under control (induce remission).

It is not known if budesonide rectal foam is safe and effective in children.

Who should not use budesoniderectal foam?

Do not use budesonide rectal foam if you are allergic to budesonide or any of the ingredients in budesonide rectal foam. See the end of this leaflet for a complete list of ingredients in budesonide rectal foam.

What should I tell my healthcare provider before using budesoniderectal foam?

Before you use budesoniderectal foam, tell your healthcare provider about all of your medical conditions, including if you:

- have liver problems.
- are planning to have surgery.
- have chicken pox or measles or have recently been near anyone with chicken pox or measles.
- have an infection.
- have or had a family history of diabetes, cataracts or glaucoma.
- have or had tuberculosis.
- have high blood pressure (hypertension).
- have decreased bone mineral density (osteoporosis).
- have stomach ulcers.
- are pregnant or plan to become pregnant. It is not known if budesonide rectal foam may harm your unborn baby. Tell your healthcare provider if you are pregnant or think you are pregnant.
- are breastfeeding or plan to breastfeed. Budesonide rectal foam can pass into your breast milk and may harm your baby. You and your healthcare provider should decide if you will use budesonide rectal foam or breastfeed. You should not do both.

Tell your healthcare provider about all the medicines you take, including prescription and over-the-counter medicines, vitamins, and herbal supplements. Budesonide rectal foam and other medicines may affect each other causing side effects. Especially tell your healthcare provider if you take another medicine that contains corticosteroids for other conditions, such as allergies or asthma.

Know the medicines you take. Keep a list of them to show your healthcare provider and pharmacist when you get a new medicine.

How should I use budesoniderectal foam?

See the “Instructions for Use” at the end of this Patient Information for detailed information about the right way to use budesoniderectal foam.

- Use budesonide rectal foam exactly as your healthcare provider tells you to use it.
- Budesoniderectal foam should only be used rectally (through the anus). Do not take budesonide rectal foam by mouth.
- Warm the budesonide rectal foam canister by holding it in your hands while shaking it (vigorously) for 10 to 15 seconds.
- Budesonide rectal foam is used twice a day for the first 2 weeks of treatment (in the morning and in the evening). After 2 weeks, use budesonide rectal foam 1 time a day in the evening, before bedtime for 4 weeks.
- If you use too much budesonide rectal foam, call your healthcare provider right away.
- You should stop using budesonide rectal foam before preparing for a colonoscopy. Call your healthcare provider before restarting budesonide rectal foam after your colonoscopy.

What should I avoid while using budesoniderectal foam?

- Do not eat grapefruit or drink grapefruit juice while using budesonide rectal foam. Eating grapefruit or drinking grapefruit juice can increase the level of budesonide rectal foam in your blood.
- Budesonide rectal foam is flammable. Avoid fire, flame and smoking during and right after using budesonide rectal foam.

What are the possible side effects of budesoniderectal foam?

Budesoniderectal foam may cause serious side effects, including:

- Effects of having too much corticosteroid medicine in your blood (hypercorticism). Long-time use of budesonide rectal foam can cause you to have too much glucocorticosteroid medicine in your blood. Tell your healthcare provider if you have any of the following signs and symptoms of hypercorticism:
- acne
- bruise easily
- rounding of your face (moon face)
- ankle swelling
- thicker or more hair on your body and face
- a fatty pad or hump between your shoulders (buffalo hump)
- pink or purple stretch marks on the skin of your abdomen, thighs, breasts and arms
- Adrenal suppression. When budesonide rectal foam is used for a long period of time (chronic use), the adrenal glands may not make enough steroid hormones (adrenal suppression). Tell your healthcare provider if you are under stress or have any symptoms of adrenal suppression during treatment with budesonide rectal foam including:
  - tiredness
  - weakness
  - nausea
  - vomiting
  - low blood pressure
- Immune system effects and a higher chance of infections. Budesonide rectal foam may weaken your immune system. Taking medicines that weaken your immune system makes you more likely to get infections. Avoid contact with people who have contagious diseases such as chicken pox or measles while using budesonide rectal foam.
Tell your healthcare provider about any signs or symptoms of infection during treatment with budesonide rectal foam, including:

- fever

- chills

- aches

- feeling tired

- pain

- nausea or vomiting

- Worsening of allergies. If you take certain other corticosteroid medicines to treat allergies, switching to budesonide rectal foam may cause your allergies to come back. These allergies may include eczema (a skin disease) or inflammation inside your nose (rhinitis). Tell your healthcare provider if any of your allergies become worse while using budesonide rectal foam.

The most common side effects of budesonide rectal foam include:

- decreased blood cortisol levels
- adrenal insufficiency
- nausea

Tell your healthcare provider if you have any side effect that bothers you or that does not go away.

These are not all the possible side effects of budesonide rectal foam. For more information, ask your healthcare provider or pharmacist.

Call your doctor for medical advice about side effects. You may report side effects to FDA at 1-800-FDA-1088.

How should I store budesoniderectal foam?

- Store budesonide rectal foam at room temperature, between 68° to 77°F (20° to 25°C).
- Do not store the budesonide rectal foam container near heat or store at temperatures above 120°F (49°C).
- Do not puncture or burn the budesonide rectal foam canister.
- Do not refrigerate.

Keep budesoniderectal foam and all medicines out of reach of children.

General information about the safe and effective use of budesoniderectal foam.

Medicines are sometimes prescribed for purposes other than those listed in a Patient Information leaflet. Do not use budesonide rectal foam for a condition for which it was not prescribed. Do not give budesonide rectal foam to other people, even if they have the same symptoms you have. It may harm them.

This Patient Information leaflet summarizes the most important information about budesonide rectal foam. If you would like more information, talk with your healthcare provider. You may ask your healthcare provider or pharmacist for information about budesonide rectal foam that is written for health professionals.

For more information, call 1-800-321-4576.

What are the ingredients in budesoniderectal foam?

Active ingredient: budesonide

Inactive ingredients: cetyl alcohol, citric acid monohydrate, edetate disodium, emulsifying wax, polyoxyl (10) stearyl ether, propylene glycol, and purified water

Propellant: n-butane, isobutane, and propane

Distributed by:

Oceanside Pharmaceuticals, a division of

Bausch Health US, LLC

Bridgewater, NJ 08807 USA

Manufactured by:

ASM Aerosol-Service AG

Industriestrasse 11

CH-4313 Möhlin Switzerland

Product marketed and distributed under license from Dr. Falk Pharma.

© 2021 Bausch Health Companies Inc. or its affiliates

This Patient Information has been approved by the U.S. Food and Drug Administration.

9767800 EX00245

Revised: 10/2021

Instructions for Use

Budesonide rectal foam

Read the Patient Information and Instructions for Use that comes with budesoniderectal foam before you start using it and each time you get a refill. There may be new information. This information does not take the place of talking to your healthcare provider about your medical condition or treatment. Talk to your healthcare provider if you have any questions.

Before using budesoniderectal foam, you should use the bathroom to empty your bowels.

You may use budesoniderectal foam while in a standing position, in a lying position, or in a sitting position (for example, while using the toilet).

Applicators should be used only 1 time. You should use a new applicator for each dose.

Figure A

Each kit contains (See Figure A):

- Complete Prescribing Information
- Patient Information and Instructions for Use
- 2 canisters containing 14 doses each
- 4 trays of single-use applicators (7 applicators per tray)
- Applicator throw away (disposal) bags for use after each dose

Preparing to use budesoniderectal foam

Figure B

Step 1: Twist Safety Tab to Remove

Before the first use, remove the safety tab from

under the pump dome (See Figure B).

The canister cannot be used if safety tab is not removed.

Step 2: Attach the Applicator

The applicators are in a tray. Hold the tray firmly and pull to remove 1 applicator.

Push the applicator firmly onto the nozzle of the canister (See Figure C).

Each applicator is coated with a lubricant. If needed, you can apply an additional lubricant, such as Vaseline (petrolatum, petroleum jelly).

Figure C

Step 3: Align Notch to Nozzle

To unlock the canister, twist the dome on the top of the canister until the semicircular notch underneath the dome is in line with the nozzle (See Figure D).

Figure D

Step 4: Warm and Shake Canister

Warm the canister by holding it in your hands while shaking it vigorously for 10 to 15 seconds (See Figure E).

Figure E

Step 5: Turn the Canister Upside Down

Place your pointer finger (forefinger) on the top of pump dome and then turn the canister upside down (See Figure F).

The canister will only work properly when held with the pump dome pointing down.

Figure F

Step 6: Insert the Applicator into Rectum

Insert the applicator into your rectum as far as it is comfortable.

The easiest way to use budesonide rectal foam is to keep 1 foot on the floor and raise the other foot onto a firm surface such as a chair or stool (See Figure G).

Figure G

Step 7: Give a Dose of budesoniderectal foam

To give a dose of budesoniderectal foam, use your pointer finger (forefinger) to fully push down the pump dome 1 time and hold it for about 2 seconds in that position (See Figure H).

Figure H

Step 8: Release and Hold

Release finger pressure on the pump dome and hold the applicator in place for 10 to 15 seconds (See Figure I).

Figure I

Step 9: Remove the Applicator

(See Figure J)

The foam will still expand a little and may drop out of the applicator or anus.

Figure J

Step 10: Remove Applicator from Canister

Remove the applicator from the canister and place the used applicator in the applicator throw away (disposal) bag provided (See Figure K). Throw the applicator throw away (disposal) bag away in your household trash.

Figure K

Step 11: Twist Notch on Dome Away from Nozzle

To prevent loss of budesonide rectal foam from the canister between uses, turn the pump dome around so that the semicircular notch faces the opposite direction to the nozzle (See Figure L).

Wash your hands with soap and water after using the budesoniderectal foam. Try not to empty your bowels until the next morning.

Figure L

Distributed by:

Oceanside Pharmaceuticals, a division of

Bausch Health US, LLC

Bridgewater, NJ 08807 USA

Manufactured by:

ASM Aerosol-Service AG

Industriestrasse 11

CH-4313 Möhlin Switzerland

Product marketed and distributed under license from Dr. Falk Pharma.

© 2021 Bausch Health Companies Inc. or its affiliates

This Instructions for Use has been approved by the U.S. Food and Drug Administration.

Revised: 10/2021

9767800
EX00245

PACKAGE/LABEL PRINCIPAL DISPLAY PANEL

NDC 68682-658-03

Rx only

BUDESONIDE RECTAL FOAM

2 mg/actuation

FOR RECTAL ADMINISTRATION ONLY, as directed
by a physician. Shake well before using.

Each canister contains 14 metered doses.
Net weight 33.4 g per canister.

OCEANSIDE
PHARMACEUTICALS

9767700